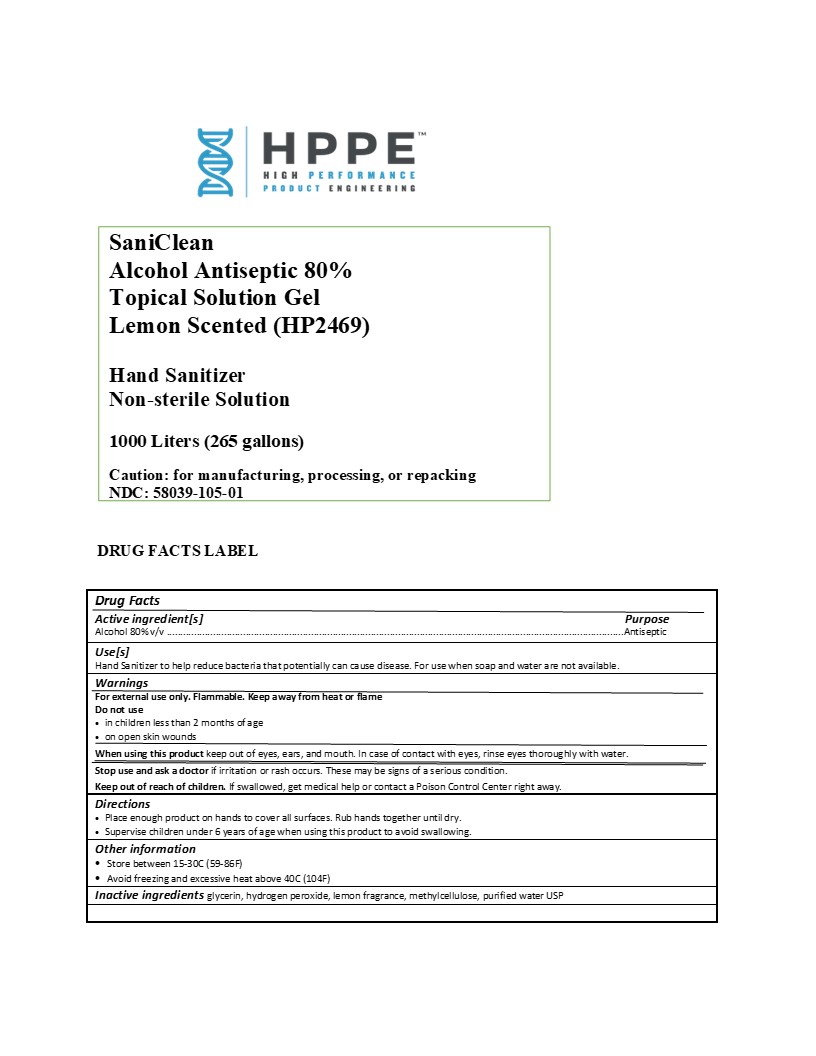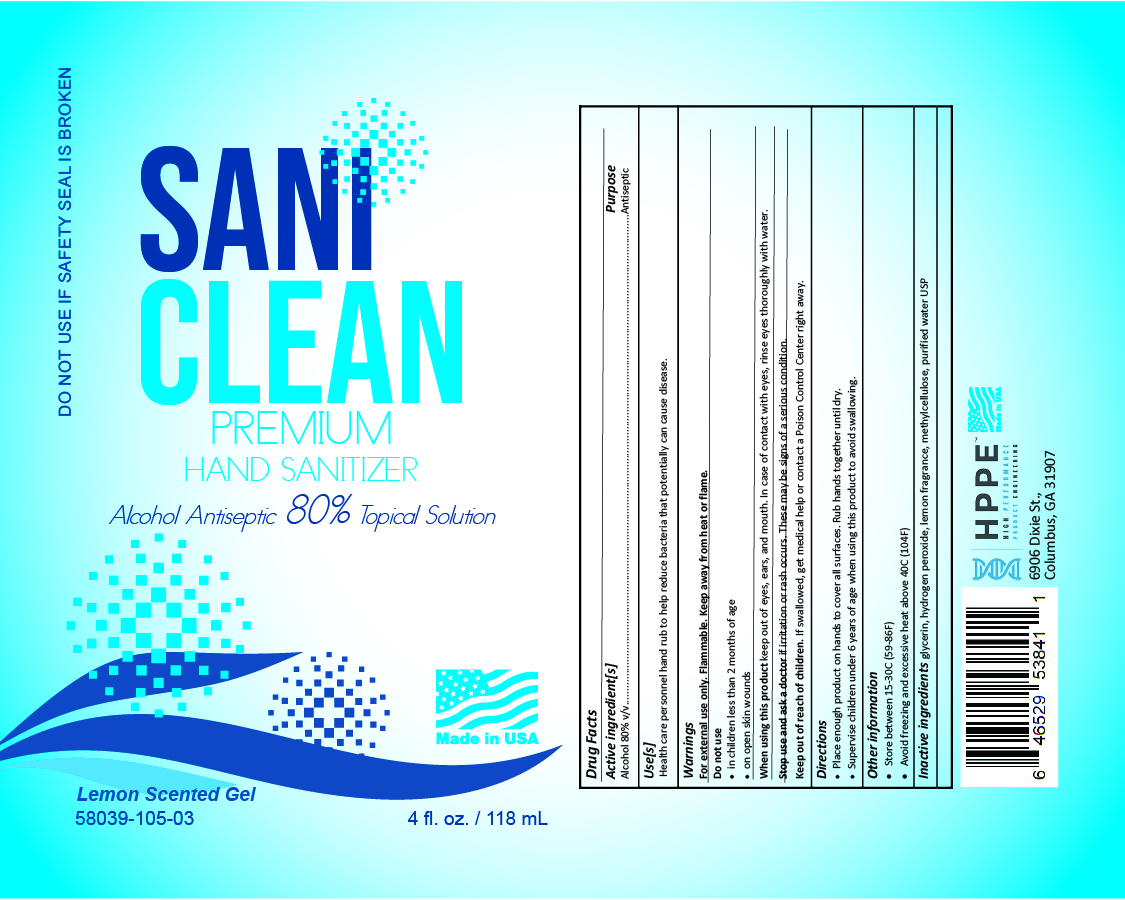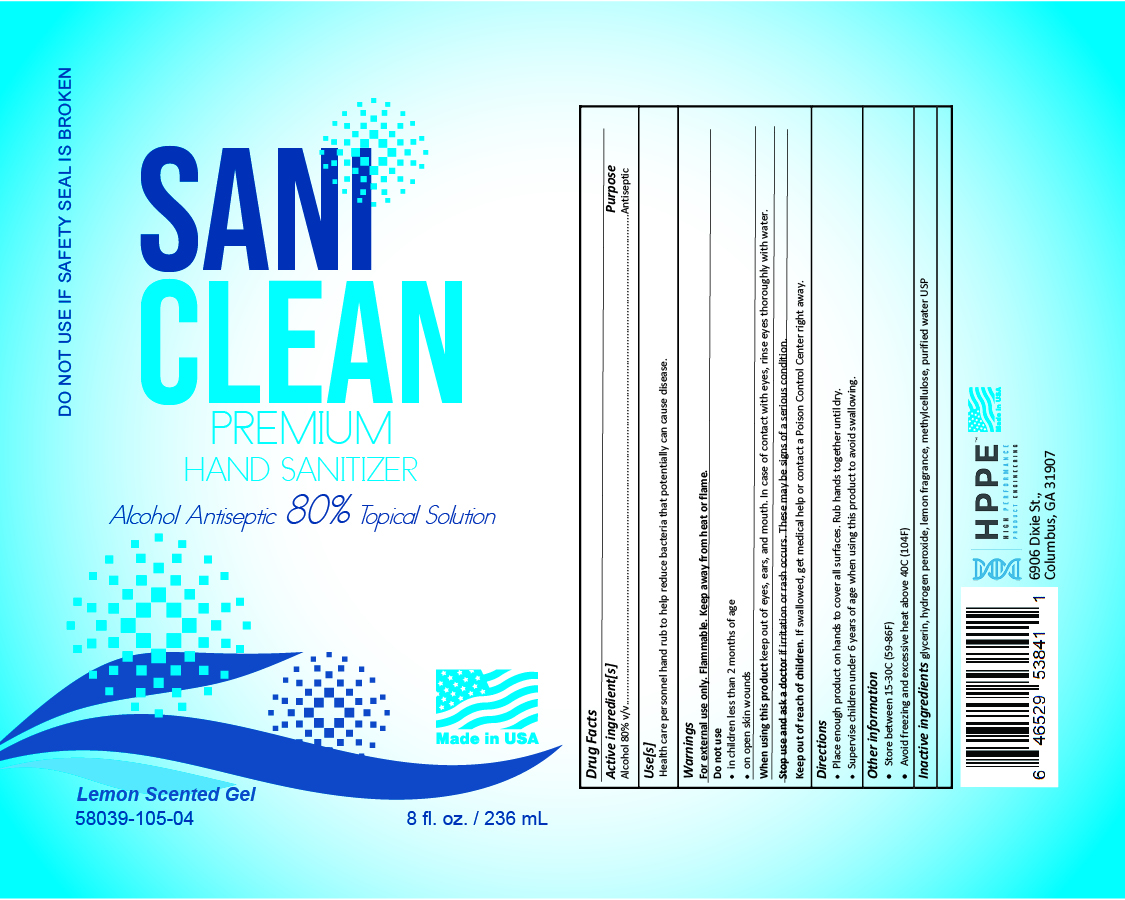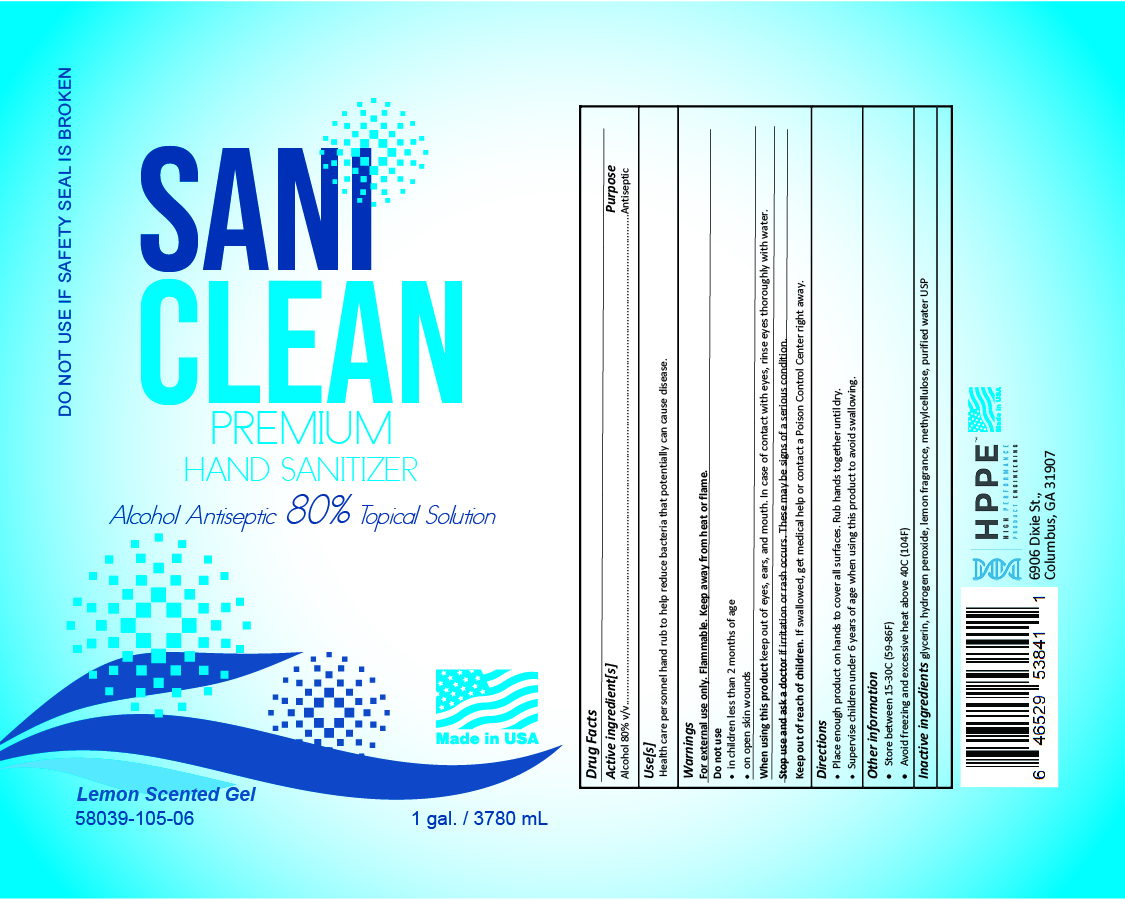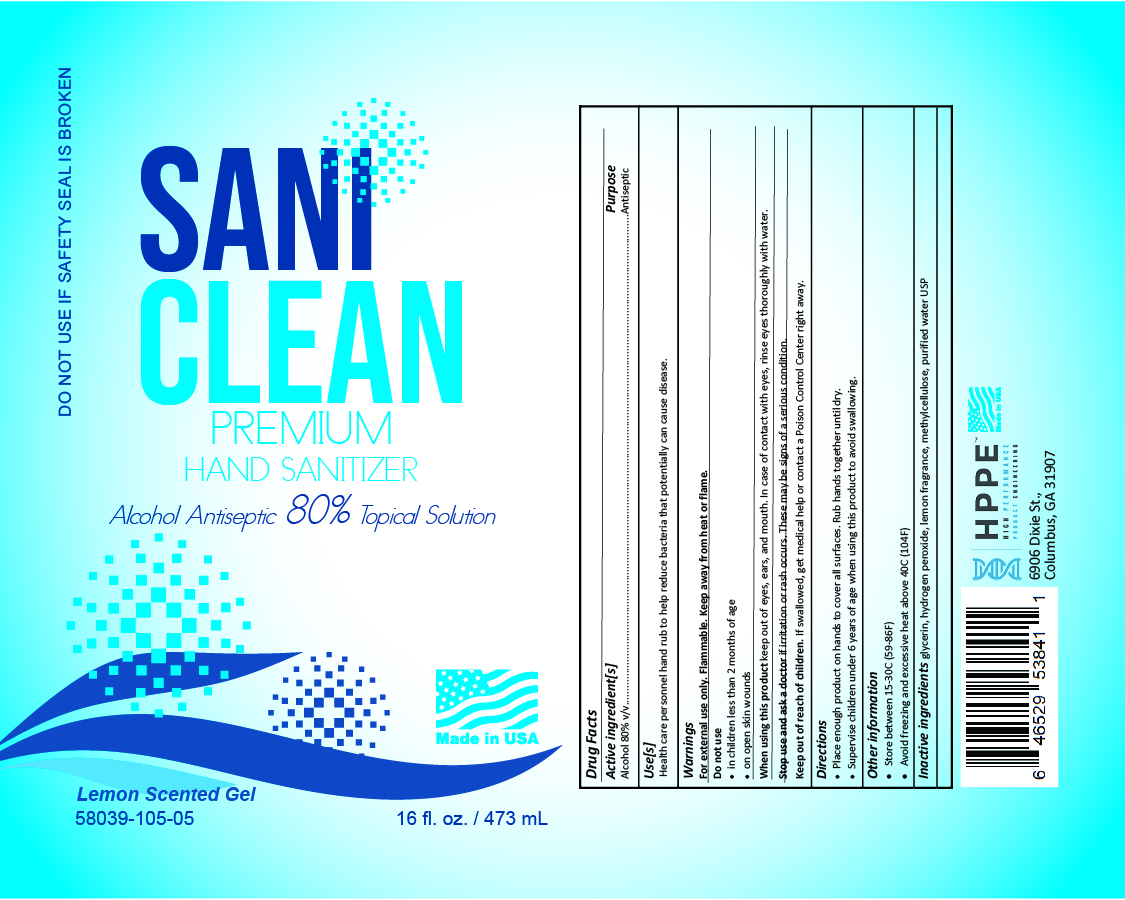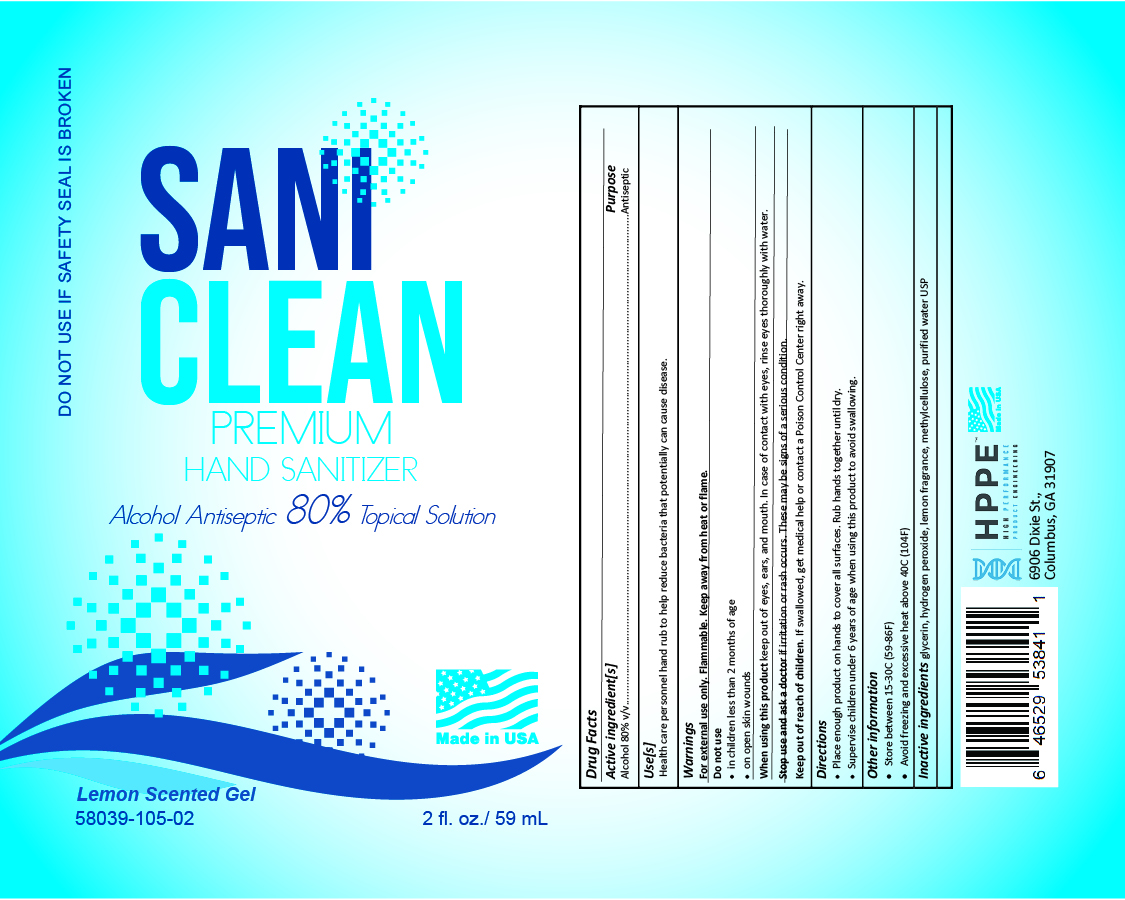 DRUG LABEL: Hand Sanitizer
NDC: 58039-105 | Form: GEL
Manufacturer: HPPE, LLC
Category: otc | Type: HUMAN OTC DRUG LABEL
Date: 20200706

ACTIVE INGREDIENTS: ALCOHOL 800 L/1000 L
INACTIVE INGREDIENTS: METHYLCELLULOSE, UNSPECIFIED 11 L/1000 L; GLYCERIN 14.5 L/1000 L; HYDROGEN PEROXIDE 1.25 L/1000 L; WATER 179.3 L/1000 L; LEMON 5 L/1000 L

HP2469 Lemon Product 58039-105

Active Ingredient(s)

Alcohol 80% v/v. Purpose: Antiseptic

Purpose

Antiseptic, Hand Sanitizer

Use

Hand Sanitizer to help reduce bacteria that potentially can cause disease. For use when soap and water are not available.

Warnings

For external use only. Flammable. Keep away from heat or flame

Do not use

- in children less than 2 months of age
- on open skin wounds

When using this product keep out of eyes, ears, and mouth. In case of contact with eyes, rinse eyes thoroughly with water.
Stop use and ask a doctor if irritation or rash occurs. These may be signs of a serious condition.
Keep out of reach of children. If swallowed, get medical help or contact a Poison Control Center right away.

Stop use and ask a doctor if irritation or rash occurs. These may be signs of a serious condition.

Keep out of reach of children. If swallowed, get medical help or contact a Poison Control Center right away.

Directions

- Place enough product on hands to cover all surfaces. Rub hands together until dry.
- Supervise children under 6 years of age when using this product to avoid swallowing.

Other information

- Store between 15-30C (59-86F)
- Avoid freezing and excessive heat above 40C (104F)

Inactive ingredients

glycerin, hydrogen peroxide, lemon fragrance, methylcellulose, purified water USP

Package Label - Principal Display Panel

1000 L NDC: 58039-105-01

0.059 L NDC: 58039-105-02

0.118 L NDC: 58039-105-03

0.236 L NDC: 58039-105-04

0.473 L NDC: 58039-105-05

3.78 L NDC: 58039-105-06